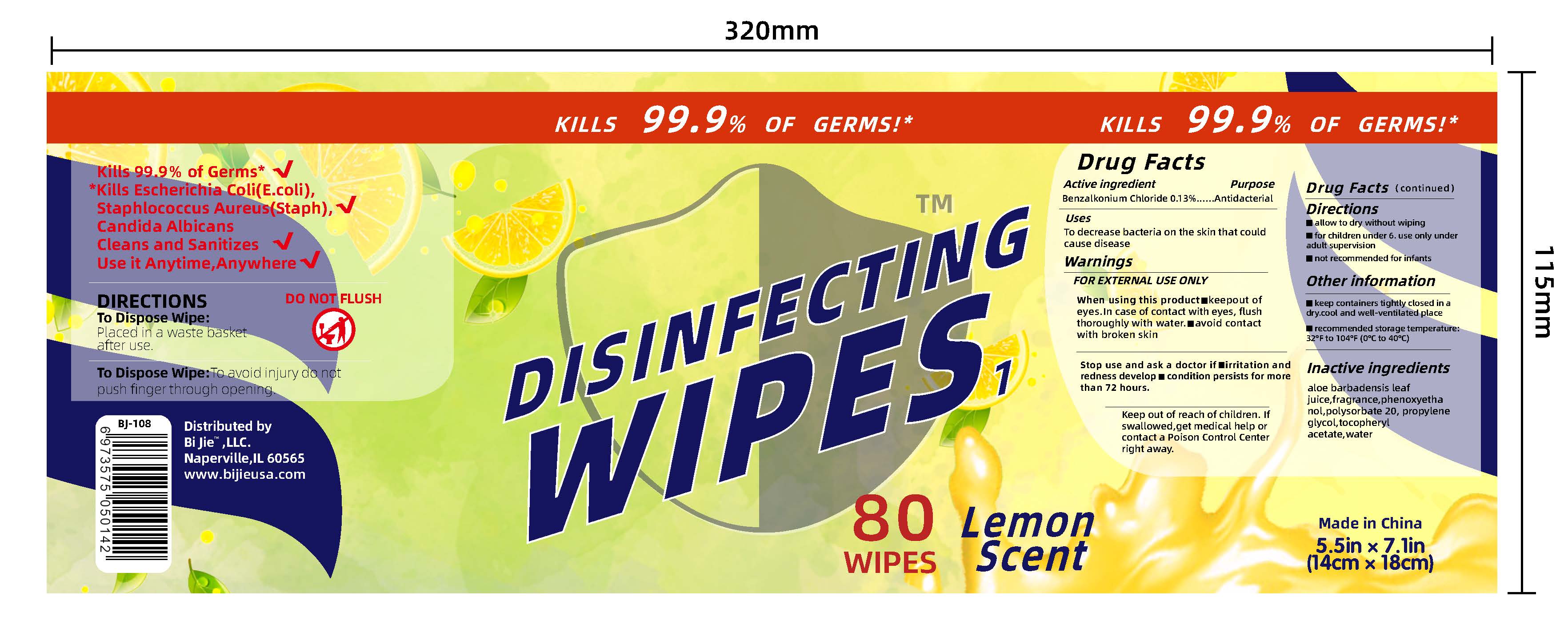 DRUG LABEL: Disinfecting Wipes
NDC: 81344-001 | Form: CLOTH
Manufacturer: BI JIE LLC
Category: otc | Type: HUMAN OTC DRUG LABEL
Date: 20210112

ACTIVE INGREDIENTS: BENZALKONIUM CHLORIDE 0.13 g/100 mL
INACTIVE INGREDIENTS: ALOE VERA LEAF; POLYSORBATE 20; ALPHA-TOCOPHEROL ACETATE; PROPYLENE GLYCOL; WATER; PHENOXYETHANOL

Disinfecting wipes

Disinfecting Wipes

Wipes containing the active ingredient are used topically and externally only.

Disinfecting Wipes

FOR EXTERNAL USE ONLY. Keep out of eyes. In case of contact with eyes, flush thoroughly with water. Avoid contact with broken skin. Stop use and ask a doctor if irritation and redness develop or such condition persists for more than 72 hours. Keep out of reach of children. If swallowed, get medical help or contact a poison control center right away.

Disinfecting Wipes

INACTIVE INGREDIENTS

Aloe Barbadensis Leaf, Fragrance, Phenoxyethanol, Polysorbate 20, Propylene Glycol, Tocopheryl Acetate, Water

Disinfecting Wipes

To decrease bacteria on skin that could cause disease. For external use only.

Disinfecting Wipes

Keep out of reach of children. If swallowed, get medical help or contact a poison control center right away. For children under 6, use only under adult supervision. Not recommended for infants.

Disinfecting Wipes

To decrease bacteria on skin that could cause disease.

Disinfecting Wipes

ACTIVE INGREDIENTS:

Benzalkonium Chloride 0.13%

Disinfecting Wipes

1L NDC: 81344-001-01